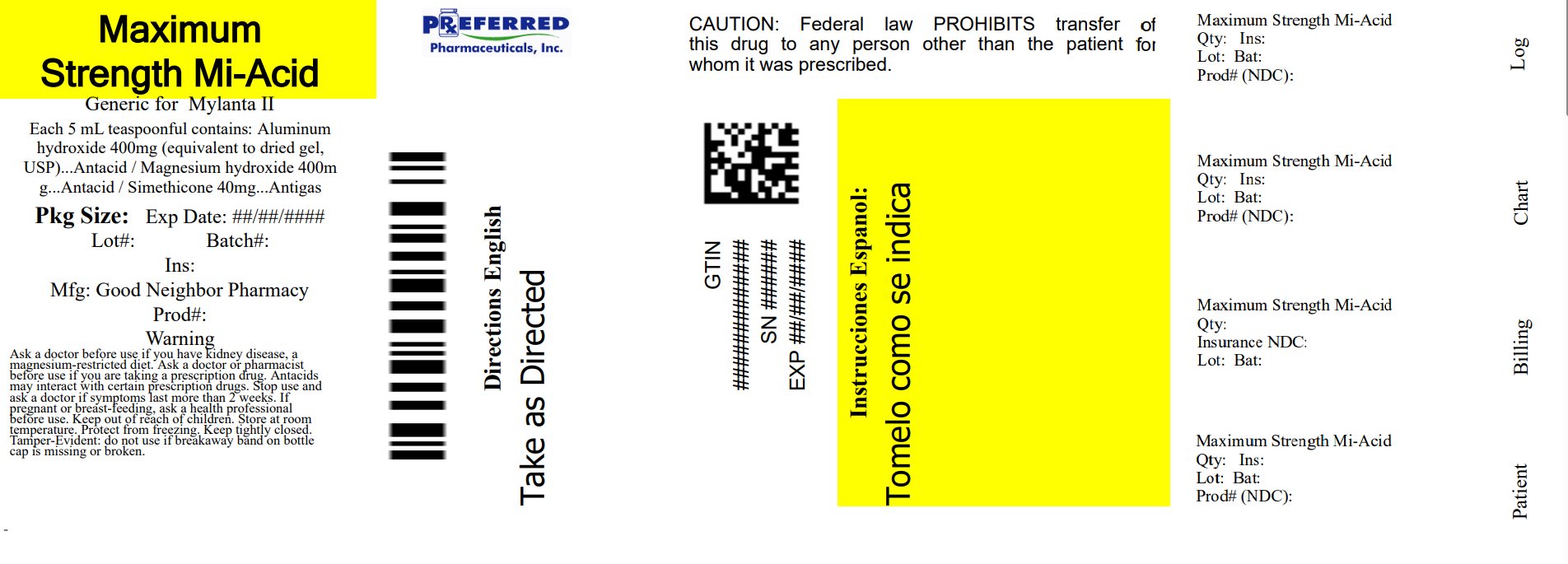 DRUG LABEL: ANTACID ANTIGAS
NDC: 68788-7641 | Form: LIQUID
Manufacturer: Preferred Pharmaceuticals, Inc.
Category: otc | Type: HUMAN OTC DRUG LABEL
Date: 20250804

ACTIVE INGREDIENTS: ALUMINUM HYDROXIDE 400 mg/5 mL; MAGNESIUM HYDROXIDE 400 mg/5 mL; DIMETHICONE, UNSPECIFIED 40 mg/5 mL
INACTIVE INGREDIENTS: BENZYL ALCOHOL; BUTYLPARABEN; CARBOXYMETHYLCELLULOSE SODIUM, UNSPECIFIED; HYPROMELLOSE, UNSPECIFIED; MICROCRYSTALLINE CELLULOSE; PROPYLPARABEN; WATER; SACCHARIN SODIUM; SORBITOL

Good Neighbor Pharmacy Antacid Anti-Gas max cherry

Active ingredients (in each 5 mL, 1 teaspoon)

Aluminum hydroxide (equivalent to dried gel, USP) 400 mg

Magnesium hydroxide 400 mg

Simethicone 40 mg

Purposes

Antacid

Antigas

Uses

relieves

- heartburn
- sour stomach
- acid indigestion
- upset stomach due to these symptoms
- symptoms of gas

Warnings

Ask a doctor before use if you have

• kidney disease

• a magnesium-restricted diet

Ask a doctor or pharmacist before use if you are presently taking a prescription drug.

Antacids may interact with certain prescription drugs.

Stop use and ask a doctor if symptoms last more than 2 weeks

If pregnant or breast-feeding, ask a health professional before use.

Keep out of reach of children. In case of accidental overdose, get medical help or contact a Poison Control Center (1-800-222-1222) immediately.

Directions

- shake well before use
- adults and children 12 years of age and older: take 2 to 4 teaspoonfuls two times a day or as directed by a doctor
- do not exceed 8 teaspoonfuls in a 24 hour period or use the maximum dosage for more than 2 weeks
- children under 12 years of age: ask a doctor

Other information

- each 5 mL teaspoonful contains: magnesium 165 mg, sodium 5 mg
- store at room temperature tightly closed
- protect from freezing

Inactive ingredients

benzyl alcohol, butylparaben, carboxymethylcellulose sodium, flavor, hypromellose, microcrystalline cellulose, propylparaben, purified water, saccharin sodium, sorbitol solution

Questions or Comments?

1-800-540-3765

package label

Relabeled by Preferred Pharmaceuticals, Inc.

Compare To Maalox® Maximum Strength active ingredients*

NDC 68788-7641-03

MAXIMUM STRENGTH

Antacid
Anti-Gas

Alumina, Magnesia, and Simethicone Oral Suspension

Fast Relief of:
• Acid Indigestion
• Heartburn
• Sour Stomach
• Pressure and Bloating
Cherry Creme Flavor

12 FL OZ (355 mL)